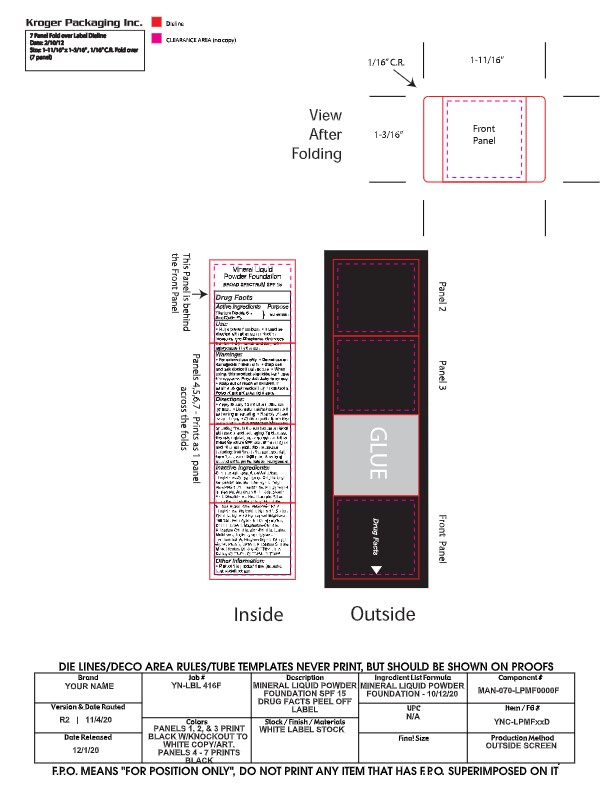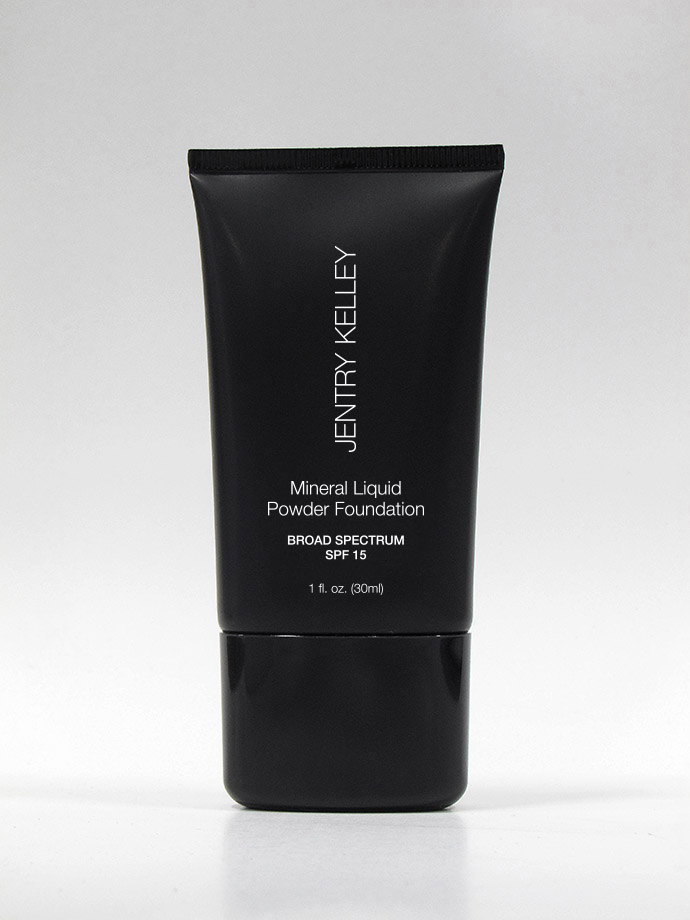 DRUG LABEL: MINERAL LP FOUNDATION  Sandy Beige
NDC: 84179-210 | Form: CREAM
Manufacturer: JENTRY KELLEY
Category: otc | Type: HUMAN OTC DRUG LABEL
Date: 20240422

ACTIVE INGREDIENTS: ZINC OXIDE 3 g/30 mL; TITANIUM DIOXIDE 6 g/30 mL
INACTIVE INGREDIENTS: FERRIC OXIDE YELLOW; FERROSOFERRIC OXIDE; BUTYLENE GLYCOL; HYALURONATE SODIUM; ALUMINUM HYDROXIDE; POTASSIUM CHLORIDE; OCTYLDODECYL NEOPENTANOATE; DIMETHICONE; DISODIUM 4,4'-BIS((4-ANILINO-6-((2-CARBAMOYLETHYL)(2-HYDROXYETHYL)AMINO)-S-TRIAZIN-2-YL)AMINO)-2,2'-STILBENEDISULFONATE; MICA; FERRIC OXIDE RED; POTASSIUM SORBATE; POLYVINYL ALCOHOL, UNSPECIFIED; MAGNESIUM CHLORIDE; ZINC CHLORIDE; SILICON DIOXIDE; SODIUM CHLORIDE; LYSINE; CYCLOMETHICONE 5; POLYGLYCERYL-4 ISOSTEARATE; WATER; HEXYL LAURATE; DIMETHICONE CROSSPOLYMER (450000 MPA.S AT 12% IN CYCLOPENTASILOXANE); METHICONE (20 CST); TRIETHOXYCAPRYLYLSILANE; CAPRYLYL GLYCOL; PHENOXYETHANOL; STEARIC ACID; TETRAHEXYLDECYL ASCORBATE; PEG/PPG-18/18 DIMETHICONE; NYLON-12; CETYL PEG/PPG-10/1 DIMETHICONE (HLB 3); TOCOPHEROL; PHYTANTRIOL; OCTYLDODECANOL; EDETATE DISODIUM; HEXYLENE GLYCOL

JENTRY KELLEY MINERAL LIQUID POWDER FOUNDATION BROAD SPECTRUM SPF 15 -Sandy Beige

Actives

Titanium Dioxide 6%

Zinc Oxide 3%

Purpose

Sunscreen

Use

Helps prevent sunburn. If used as directed with other sun protection measures (see directions), decreases the risk of skin cancer and early skin aging caused by the sun.

Warnings

For external use only. Do not use on damaged or broken skin. Stop use and ask doctor if rash occurs.

When using this product keep out of eyes. Rinse with water to remove.

Keep out of reach of children. If swallowed, get medical help, or contact a Poison Control Center right away.

Directions

Apply liberally 15 minutes before sun exposure. Use a water-resistant sunscreen if swimming or sweating. Reapply at least every 2 hours, Children under 6 months: ask a doctor.

Sun Protection Measures: Spending time in the sun increases risk of skin cancer and early aging. To decrease

this risk, regularly use a sunscreen with a Broad-Spectrum SPF value of 15 or higher and other sun protection measures including: limit time in the sun especially from 10:00 a.m. - 2:00 p.m. Wear long sleeved shirts, pants, hats, and sunglasses.

Inactive Ingredients

Cyclopentasiloxane, Aqua/Water/Eau, Dimethicone Crosspolymer, Octyldodecyl Neopentanoate, Butylene Glycol, Cetyl PEG/PPG-10/1 Dimethicone, Polyglyceryl-4 Isostearate, Aluminum Hydroxide, Stearic Acid, Dimethicone, Hexyl Laurate, Silica, Tocopherol, Tetrahexyldecyl Ascorbate, Sodium Hyaluronate, PEG/PPG-18/18 Dimethicone, Phytantriol, Nylon-12, Sodium Chloride, Nylon-12 Fluorescent Brightener 230 Salt, Polyvinylalcohol Crosspolymer, Octyldodecanol, Magnesium Chloride, Potassium Chloride, Zinc Chloride , Lysine, Methicone, Triethoxycaprylylsilane, Disodium EDTA, Hexylene Glycol, Caprylyl Glycol, Phenoxyethanol, Potassium Sorbate,Mica ,Titanium Dioxide (CI 77891), Iron Oxides (CI 77492), Iron Oxides (CI 77491), Iron Oxides (CI 77499)

Other Information

Protect this product from excessive heat and direct sun